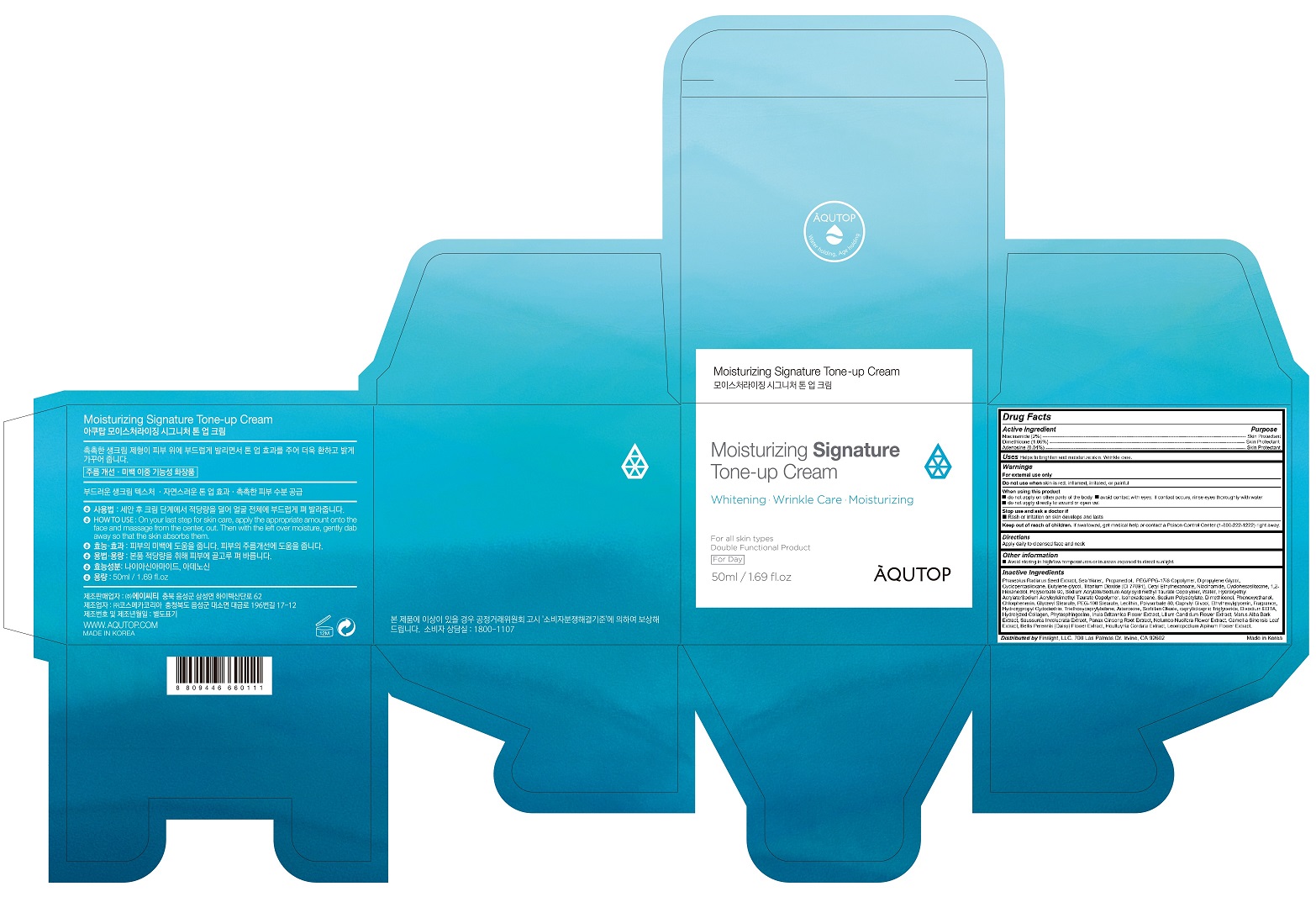 DRUG LABEL: AQUTOP Moisturizing Signature Tone-up Cream
NDC: 72419-100 | Form: CREAM
Manufacturer: ALABLE CO., LTD.
Category: otc | Type: HUMAN OTC DRUG LABEL
Date: 20180710

ACTIVE INGREDIENTS: DIMETHICONE 0.53 g/50 mL; NIACINAMIDE 1 g/50 mL; ADENOSINE 0.02 g/50 mL
INACTIVE INGREDIENTS: MUNG BEAN; PROPANEDIOL

AQUTOP Moisturizing Signature Tone-up Cream

Active Ingredient

Active Ingredient Purpose

Niacinamide (2%) ---------------------------------------------------------------------------------------------------------------------------- Skin Protectant

Dimethicone (1.06%) ----------------------------------------------------------------------------------------------------------------------- Skin Protectant

Adenosine (0.04%) -------------------------------------------------------------------------------------------------------------------------- Skin Protectant

Uses

Helps to brighten and moisturize skin. Wrinkle care.

Keep out of reach of children

If swallowed, get medical help or contact a Poison Control Center (1-800-222-1222) right away

Warnings

For external use only

Purpose

Skin Protectant

Directions

Apply daily to cleansed face and neck

When using this product

do not apply on other parts of the body avoid contact with eyes. If contact occurs, rinse eyes thoroughly with water

do not apply directly to wound or open cut

Stop use and ask a doctor if

Rash or irritation on skin develops and lasts

Inactive Ingredients

Phaseolus Radiatus Seed Extract, Sea Water, Propanediol, PEG/PPG-17/6 Copolymer, Dipropylene Glycol, Cyclopentasiloxane, Butylene glycol, Titanium Dioxide (CI 77891), Cetyl Ethylhexanoate, Cyclohexasiloxane, 1,2-Hexanediol, Polysorbate 60, Sodium Acrylate/Sodium Acryloyldimethyl Taurate Copolymer, Water, Hydroxyethyl Acrylate/Sodium Acryloyldimethyl Taurate Copolymer, Isohexadecane, Sodium Polyacrylate, Dimethiconol, Phenoxyethanol, Chlorphenesin, Glyceryl Stearate, PEG-100 Stearate, Lecithin, Polysorbate 80, Caprylyl Glycol, Ethylhexylglycerin, Fragrance, Hydroxypropyl Cydodextrin, Triethoxycaprylylsilane, Sorbitan Oleate, caprylic/capric Triglyceride, Disodium EDTA, Hydrolyzed Collagen, Phytosphingosine, Inula Britannica Flower Extract, Lilium Candidum Flower Extract, Marus Alba Bark Extract, Saussurea Involucrata Extract, Panax Ginseng Root Extract, Nelumbo Nucifera Flower Extract, Camellia Sinensis Leaf Extract, Bellis Perennis (Daisy) Flower Extract, Houttuynia Cordata Extract, Leontopodium Alpinum Flower Extract.